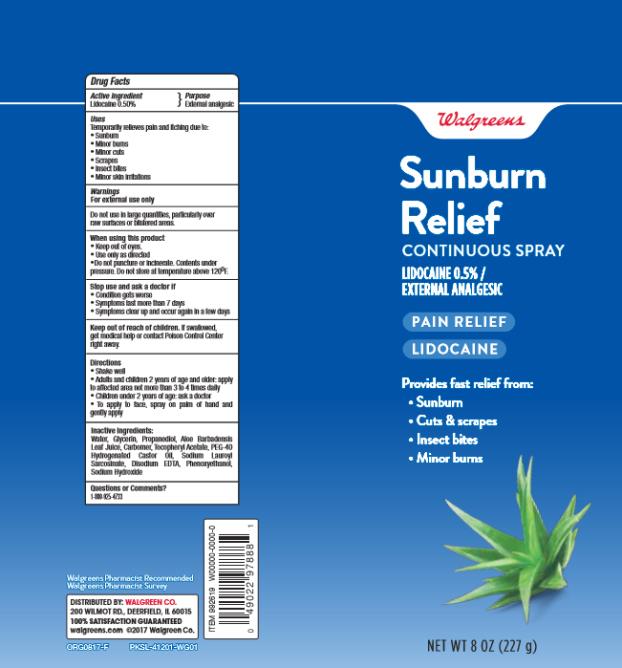 DRUG LABEL: WALG AFTRSN BURN RELIEF
NDC: 0363-9919 | Form: SPRAY
Manufacturer: Walgreen Company
Category: otc | Type: HUMAN OTC DRUG LABEL
Date: 20171005

ACTIVE INGREDIENTS: LIDOCAINE HYDROCHLORIDE 0.5 mg/100 mg
INACTIVE INGREDIENTS: WATER; GLYCERIN; ALOE VERA LEAF; CARBOXYPOLYMETHYLENE; ALPHA-TOCOPHEROL ACETATE; POLYOXYL 40 HYDROGENATED CASTOR OIL; SODIUM LAUROYL SARCOSINATE; EDETATE DISODIUM ANHYDROUS; PHENOXYETHANOL; SODIUM HYDROXIDE

WAG Aftrsn Burn Relief Spray 8oz

Product

WALGREENS AFTERSUN BURN RELIEF SPRAY

Active Ingredients

Lidocaine Hydrochloride 0.5%

Purpose

Topical Anesthetic

Uses:

- Temporary relief of pain and itching
- Helps to relieve and soothe pain from sunburn, minor burns, skin irritations, scrapes, insect bites.

Warnings:

For external use only

Do not use

in large quantities, particularly over raw surfaces or areas with blisters.

When using this product:

- Avoid contact with eyes.

Keep out of reach of children.

If swallowed, get medical help or contact a Poison Control Center right away.

Directions:

- Adults and children 2 years or older: apply to affected area not more than 3-4 times daily.
- Children under 2 years of age: do not use; ask a doctor.

Inactive Ingredients

Deionized Water, Glycerin, Propanediol, Aloe Barbadensis Leaf Juice, Carbomer, Tocopherol Acetate, PEG-40 Hydrogenated Castor Oil, Sodium Lauroyl Sarcosinate, Disodium EDTA, Phenoxyethanol, Sodium Hydroxide

Questions or comments?

www.walgreens.com or call toll free 1-800-XXX-XXXX

PRINCIPAL DISPLAY PANEL

Walgreens
Sunburn Relief
CONTINUOUS SPRAY
LIDOCAINE 0.5% /
EXTERNAL ANALGESIC
PAIN RELIEF
LIDOCAINE
8 OZ (227 g)